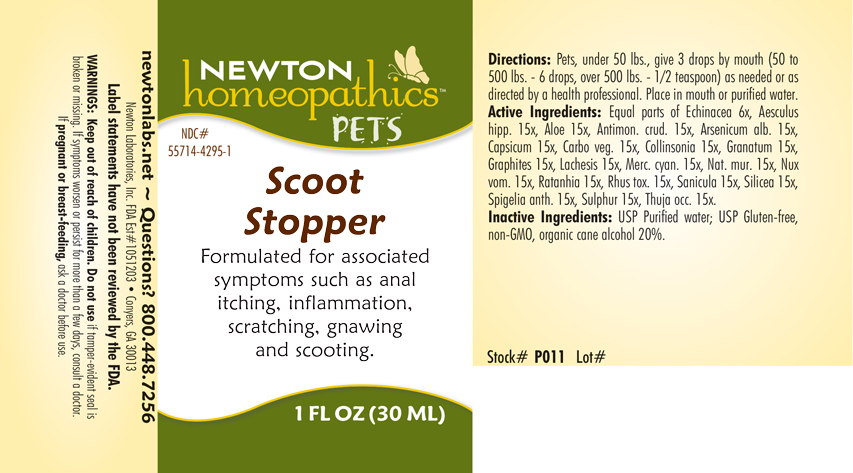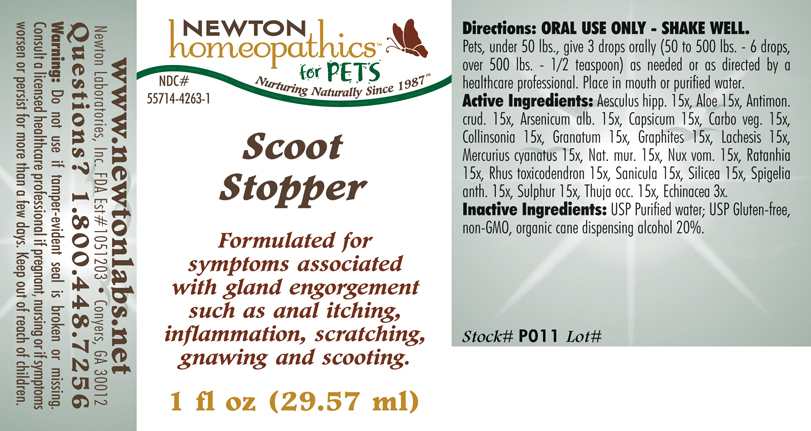 DRUG LABEL: Scoot Stopper
NDC: 55714-4263 | Form: LIQUID
Manufacturer: Newton Laboratories, Inc.
Category: homeopathic | Type: OTC ANIMAL DRUG LABEL
Date: 20190114

ACTIVE INGREDIENTS: Horse Chestnut 15 [hp_X]/1 mL; Aloe 15 [hp_X]/1 mL; Antimony Trisulfide 15 [hp_X]/1 mL; Arsenic Trioxide 15 [hp_X]/1 mL; Capsicum 15 [hp_X]/1 mL; Activated Charcoal 15 [hp_X]/1 mL; Collinsonia Canadensis Root 15 [hp_X]/1 mL; Punica Granatum Root Bark 15 [hp_X]/1 mL; Graphite 15 [hp_X]/1 mL; Lachesis Muta Venom 15 [hp_X]/1 mL; Mercuric Cyanide 15 [hp_X]/1 mL; Sodium Chloride 15 [hp_X]/1 mL; Strychnos Nux-vomica Seed 15 [hp_X]/1 mL; Krameria Lappacea Root 15 [hp_X]/1 mL; Toxicodendron Pubescens Leaf 15 [hp_X]/1 mL; Sanicula Europaea Leaf 15 [hp_X]/1 mL; Silicon Dioxide 15 [hp_X]/1 mL; Spigelia Anthelmia 15 [hp_X]/1 mL; Sulfur 15 [hp_X]/1 mL; Thuja Occidentalis Leafy Twig 15 [hp_X]/1 mL; Echinacea, Unspecified 3 [hp_X]/1 mL
INACTIVE INGREDIENTS: Alcohol

Scoot Stopper

PRODUCT NAME & INDICATIONS SECTION

Scoot Stopper Formulated for associated symptoms such as anal itching, inflammation, scratching, gnawing and scooting.

DIRECTIONS SECTION

Directions: Pets under 50 lbs. give 3 drops by mouth (50 lbs. to 500 lbs.- 6 drops, over 500 lbs. - 1/2 teaspoon) as needed or as directed by a health professional. Place in mouth or purified water.

ACTIVE INGREDIENT SECTION

Equal parts of Echinacea 6x, Aesculus hipp. 15x, Aloe 15x, Antimon. crud. 15x, Arsenicum alb. 15x, Capsicum 15x, Carbo veg. 15x, Collinsonia 15x, Granatum 15x, Graphites 15x, Lachesis 15x, Mercurius cyan. 15x, Nat. mur. 15x, Nux vom. 15x, Ratanhia 15x, Rhus tox. 15x, Sanicula 15x, Silicea 15x, Spigelia anth.15x, Sulphur 15x, Thuja occ. 15x.

INACTIVE INGREDIENT SECTION

USP Purified water; USP Gluten-free, non-GMO, organic cane alcohol 20%.

QUESTIONS SECTION

newtonlabs.net - Questions? 800.448.7256
Newton Laboratories, Inc. FDA Est # 1051203 - Conyers, GA 30013

WARNINGS SECTION

Warnings: Do not use if tamper-evident seal is broken or missing. If symptoms worsen or persist for more than a few days, consult a doctor. If pregnant or breast-feeding, ask a doctor before use.

PREGNANCY OR BREAST FEEDING SECTION

If pregnant or breast-feeding, ask a doctor before use.

OUT OF REACH OF CHILDREN SECTION

Keep out of reach of Children.